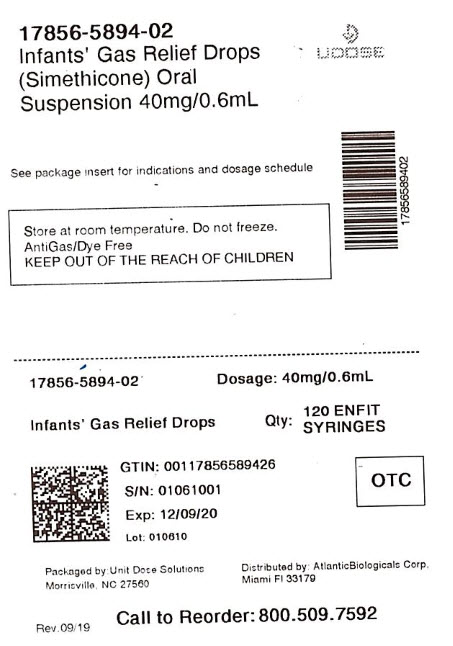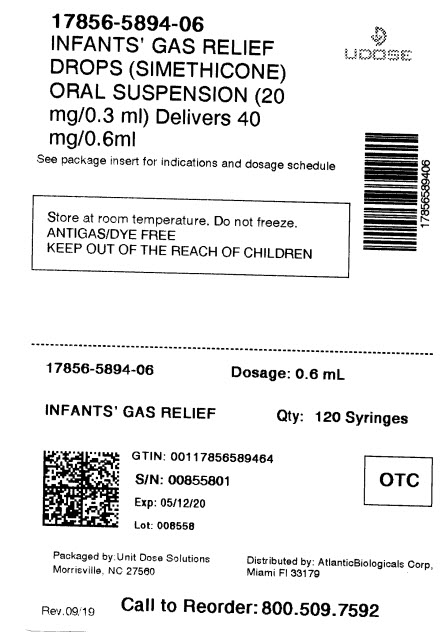 DRUG LABEL: Infants Gas Relief
NDC: 17856-5894 | Form: SUSPENSION/ DROPS
Manufacturer: Atlantic Biologicals Corps
Category: otc | Type: HUMAN OTC DRUG LABEL
Date: 20210630

ACTIVE INGREDIENTS: DIMETHICONE 20 mg/0.3 mL
INACTIVE INGREDIENTS: CARBOXYMETHYLCELLULOSE SODIUM, UNSPECIFIED FORM; ANHYDROUS CITRIC ACID; MALTITOL; MICROCRYSTALLINE CELLULOSE; WATER; SODIUM BENZOATE; ANHYDROUS TRISODIUM CITRATE; XANTHAN GUM

MAJOR INFANT GAS RELIEF

Active ingredient (in each 0.3 mL)

Simethicone 20 mg

Purpose

Antigas

Use

relieves the symptoms referred to as gas

Warnings

Keep out of reach of children. in case of overdose, get medical help or contact a poison control center right away.

Directions

- shake well before using
- all dosages may be repeated as needed, after meals and at bedtime, or as directed by a physician
- do not exceed 12 doses per day
- fill enclosed dropper to recommended dosage level and dispense liquid slowly into baby's mouth, toward inner cheek
- dosage can also be mixed with 1 oz. of cool water, infant formula or other suitable liquids
- clean dropper well after each use and replace original cap

Age (years) | Weight (lbs) | Dose
infants (under 2) | under 24 | 0.3 mL
children (2 and over) | 24 and over | 0.6 mL

Other information

- TAMPER-EVIDENT: Do not use if foil seal under cap is broken or missing.
- store at room temperature
- do not freeze
- see bottom panel for lot number and expiration date

Inactive ingredients

carboxymethylcellulose sodium, citric acid, maltitol, microcrystalline cellulose, flavor, purified water, sodium benzoate, sodium citrate, xanthan gum

Questions or comments?

(800)616-2471

HOW SUPPLIED

Product: 17856-5894

NDC: 17856-5894-1 10 mL in a CUP

NDC: 17856-5894-4 1.2 mL in a DOSE PACK / 60 in a CASE